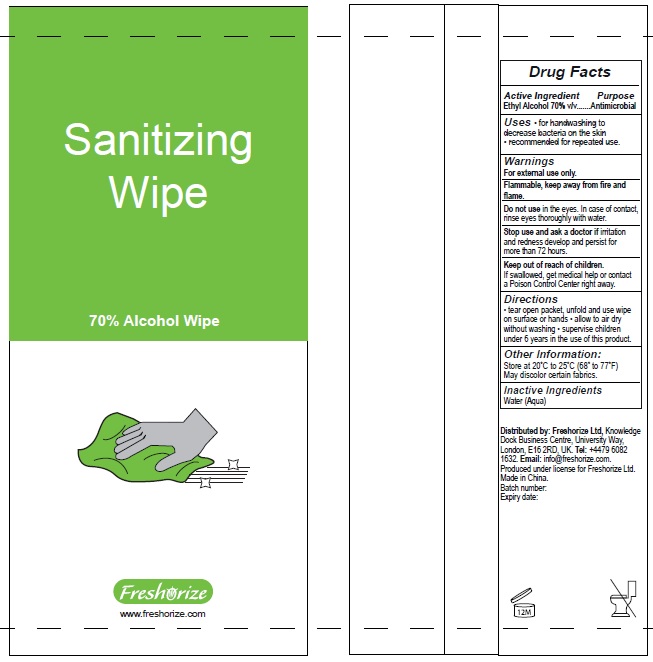 DRUG LABEL: Freshorize
NDC: 52305-500 | Form: CLOTH
Manufacturer: FRESHORIZE, LTD.
Category: otc | Type: HUMAN OTC DRUG LABEL
Date: 20200516

ACTIVE INGREDIENTS: ALCOHOL 70 mL/100 mL
INACTIVE INGREDIENTS: WATER

Sanitizing Wipe

Active lngredient

Ethyl Alcohol 70 %v/v

Purpose

Hand wipes

Uses

For handwashing to decrease bacteria on the skin - recommended for repeated use

Warnings

For external use only.

Flammable. Keep away from fire or flame.

Do not use in the eyes. In case of contact, rinse eyes thoroughly with water.

Stop use and ask a doctor if irritation and redness develop and persist for more than 72 hours.

Keep out of reach of children.

If swallowed, get medical help or contact a Poison Control Center right away.

Directions

Tear open packet, unfold and use wipe on surface or hands.

Allow to air dry without washing

Supervise children under 6 years in the use of this product

Inactives

Water (Aqua)

Keep out of reach of children.

If swallowed, get medical help or contact a Poison Control Center right away.

Other information

- Store at 20°C to 25°C (68° to 77°F)
- May discolor certain fabrics.